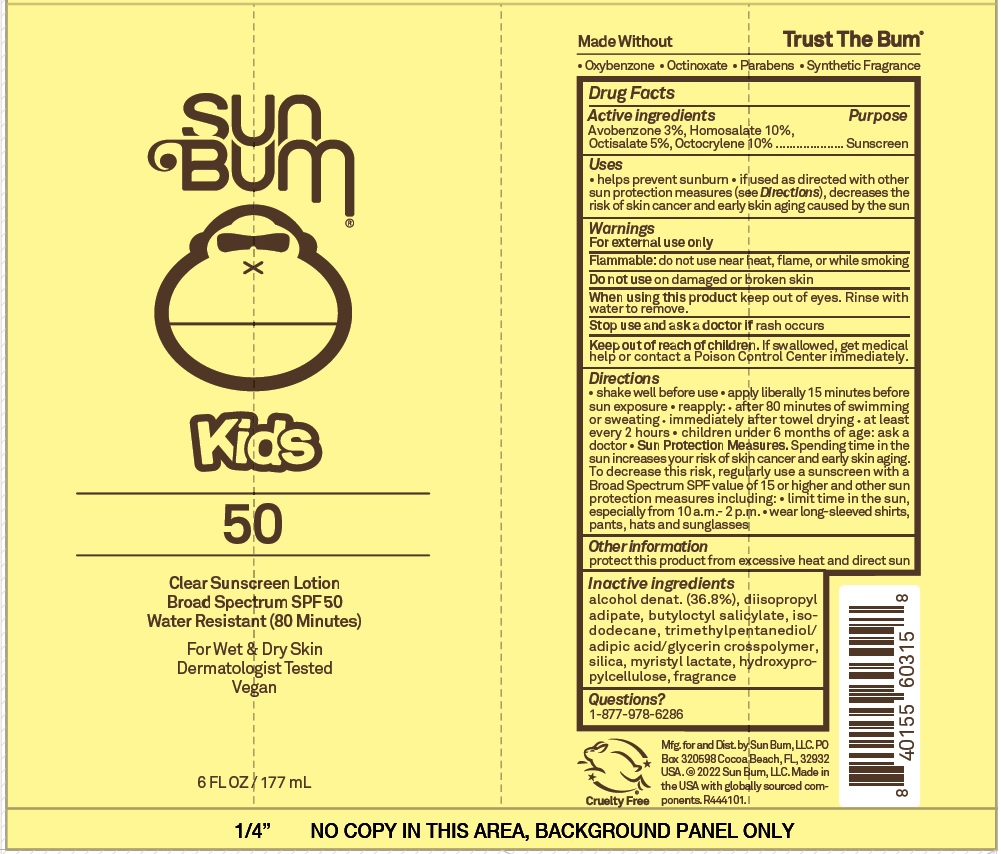 DRUG LABEL: Kids SPF 50 Sunscreen
NDC: 69039-660 | Form: LOTION
Manufacturer: Sun Bum LLC
Category: otc | Type: HUMAN OTC DRUG LABEL
Date: 20221031

ACTIVE INGREDIENTS: AVOBENZONE 30 mg/1 mL; HOMOSALATE 100 mg/1 mL; OCTISALATE 50 mg/1 mL; OCTOCRYLENE 100 mg/1 mL
INACTIVE INGREDIENTS: ALCOHOL; DIISOPROPYL ADIPATE; BUTYLOCTYL SALICYLATE; ISODODECANE; SILICON DIOXIDE; MYRISTYL LACTATE; HYDROXYPROPYL CELLULOSE, UNSPECIFIED

Kids SPF 50 Sunscreen Lotion

Active ingredients

Avobenzone 3%, Homosalate 10%,
Octisalate 5%, Octocrylene 10%

Purpose

Sunscreen

Uses

• helps prevent sunburn • if used as directed with other sun protection measures (see Directions), decreases the risk of skin cancer and early skin aging caused by the sun

Warnings

For external use only

Flammable: do not use near heat, flame, or while smoking

Do not use

on damaged or broken skin

When using this product

keep out of eyes. Rinse with water to remove.

Stop use and ask a doctor if

rash occurs

Keep out of reach of children.

If swallowed, get medical help or contact a Poison Control Center immediately.

Directions

• shake well before use • apply liberally 15 minutes before sun exposure • reapply: • after 80 minutes of swimming or sweating • immediately after towel drying • at least every 2 hours • children under 6 months of age: ask a doctor • Sun Protection Measures. Spending time in the
sun increases your risk of skin cancer and early skin aging. To decrease this risk, regularly use a sunscreen with a Broad Spectrum SPF value of 15 or higher and other sun protection measures including: • limit time in the sun, especially from 10 a.m.- 2 p.m. • wear long-sleeved shirts, pants, hats and sunglasses

Other information

protect this product from excessive heat and direct sun

Inactive ingredients

alcohol denat. (36.8%), diisopropyl adipate, butyloctyl salicylate, isododecane, trimethylpentanediol/ adipic acid/glycerin crosspolymer, silica, myristyl lactate, hydroxypropylcellulose, fragrance

Questions?

1-877-978-6286